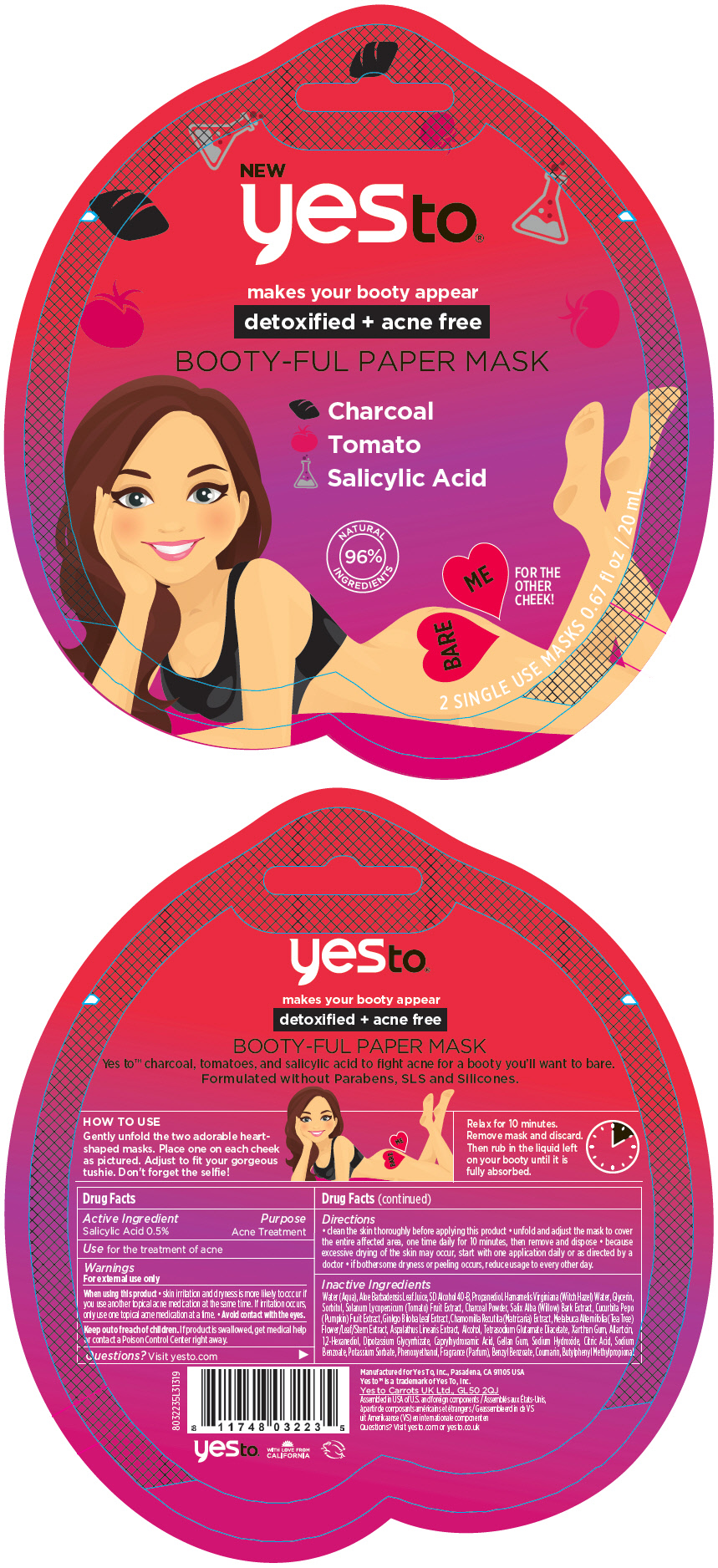 DRUG LABEL: Yes To Booty-Ful Paper Mask - detoxified plus acne-free
NDC: 69840-020 | Form: CLOTH
Manufacturer: Yes To, Inc.
Category: otc | Type: HUMAN OTC DRUG LABEL
Date: 20190429

ACTIVE INGREDIENTS: SALICYLIC ACID 5 mg/1 mL
INACTIVE INGREDIENTS: ALOE VERA LEAF; WATER; HAMAMELIS VIRGINIANA TOP WATER; PROPANEDIOL; ALLANTOIN; GLYCERIN; ACTIVATED CHARCOAL; SOLANUM LYCOPERSICUM; MELALEUCA ALTERNIFOLIA LEAF; SORBITOL; TETRASODIUM GLUTAMATE DIACETATE; ENOXOLONE DIPOTASSIUM; XANTHAN GUM; CAPRYLHYDROXAMIC ACID; GELLAN GUM (LOW ACYL); SALIX ALBA BARK; GINKGO; PHENOXYETHANOL; PUMPKIN; MATRICARIA CHAMOMILLA LEAF; ASPALATHUS LINEARIS LEAF; CITRIC ACID MONOHYDRATE; SODIUM HYDROXIDE; 1,2-HEXANEDIOL; SODIUM BENZOATE; POTASSIUM SORBATE; ALCOHOL

Yes To® Booty-Ful Paper Mask - detoxified + acne-free

Drug Facts

Active Ingredient

Salicylic Acid 0.5%

Purpose

Acne Treatment

Use

for the treatment of acne

Warnings

For external use only

When using this product

- skin irritation and dryness is more likely to occur if you use another topical acne medication at the same time. If irritation occurs, only use one topical acne medication at a time.
- Avoid contact with the eyes.

Keep out of reach of children. If product is swallowed, get medical help or contact a Poison Control Center right away.

Questions?

Visit yesto.com

Directions

- clean the skin thoroughly before applying this product
- unfold and adjust the mask to cover the entire affected area, one time daily for 10 minutes, then remove and dispose
- because excessive drying of the skin may occur, start with one application daily or as directed by a doctor
- if bothersome dryness or peeling occurs, reduce usage to every other day.

Inactive Ingredients

Water (Aqua), Aloe Barbadensis Leaf Juice, SD Alcohol 40-B, Propanediol. Hamamelis Virginiana (Witch Hazel) Water, Glycerin, Sorbitol, Solanum Lycopersicum (Tomato) Fruit Extract, Charcoal Powder, Salix Alba (Willow) Bark Extract, Cucurbita Pepo (Pumpkin) Fruit Extract, Ginkgo Biloba Leaf Extract, Chamomilla Recutita (Matricaria) Extract, Melaleuca Alternifolia (Tea Tree) Flower/Leaf/Stem Extract, Aspalathus Linearis Extract, Alcohol, Tetrasodium Glutamate Diacetate, Xanthan Gum, Allantoin, 1,2-Hexanediol, Dipotassium Glycyrrhizate, Caprylhydroxamic Acid, Gellan Gum, Sodium Hydroxide, Citric Acid, Sodium Benzoate, Potassium Sorbate, Phenoxyethanol, Fragrance (Parfum), Benzyl Benzoate, Coumarin, Butylphenyl Methylpropional.

PRINCIPAL DISPLAY PANEL - 2 Mask Packet

NEW
yesto®

makes your booty appear
detoxified + acne free

BOOTY-FUL PAPER MASK

Charcoal
Tomato
Salicylic Acid

NATURAL
96%
INGREDIENTS

BARE
ME

FOR THE
OTHER
CHEEK!

2 SINGLE USE MASKS 0.67 fl oz / 20 mL